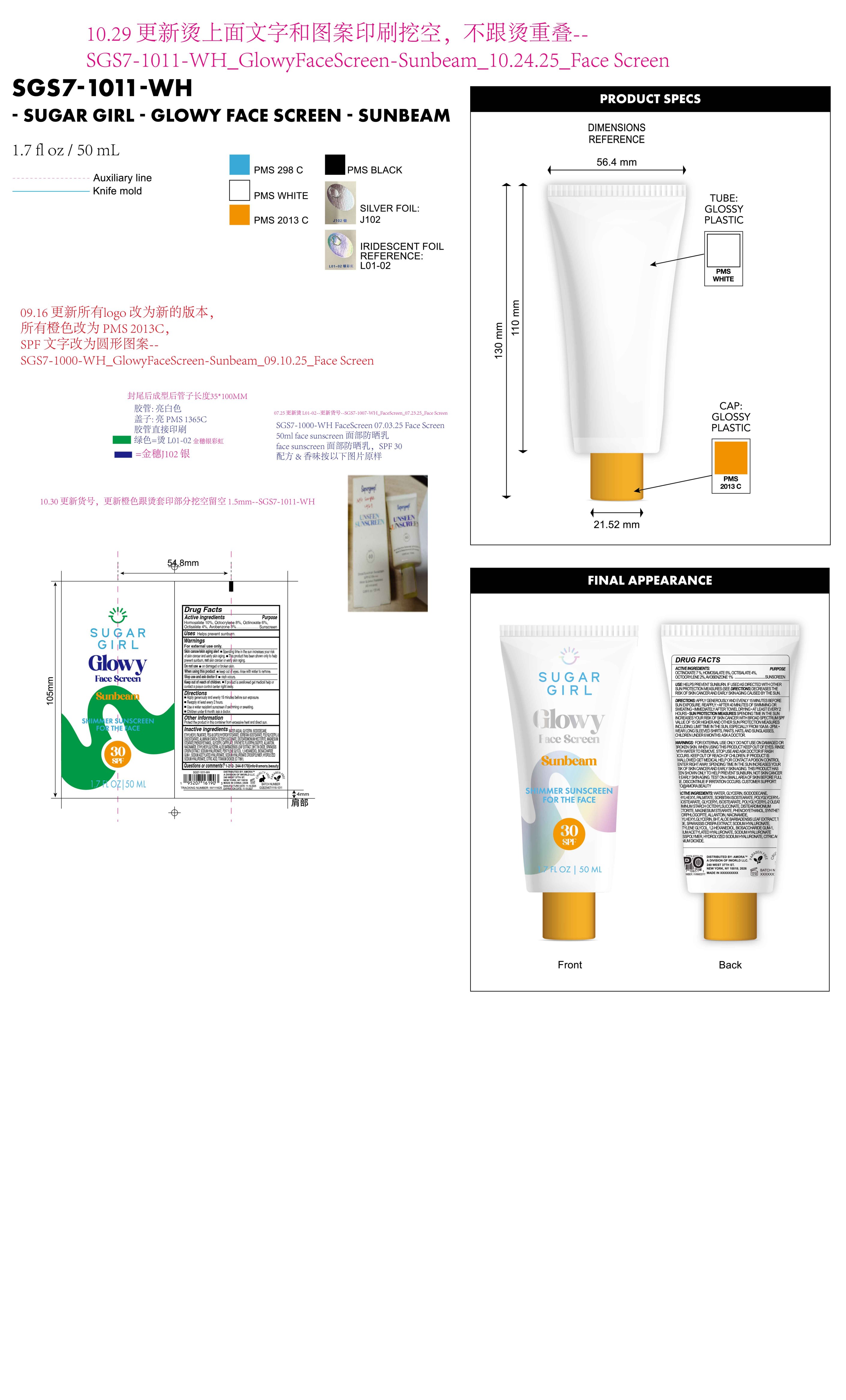 DRUG LABEL: Sugargirl Glowy face screen sunbeam shimmer sunscreen for the face SPF 30
NDC: 85161-167 | Form: LOTION
Manufacturer: Longway Technology(Guangzhou)Co.,Ltd.
Category: otc | Type: HUMAN OTC DRUG LABEL
Date: 20251204

ACTIVE INGREDIENTS: OCTISALATE 0.04 g/1 mL; OCTOCRYLENE 0.08 g/1 mL; HOMOSALATE 0.1 g/1 mL; OCTINOXATE 0.06 g/1 mL; AVOBENZONE 0.03 g/1 mL
INACTIVE INGREDIENTS: TIN OXIDE; GLYCERYL CAPRYLATE; CI 77891; ALUMINUM STARCH OCTENYLSUCCINATE; PEG-30 DIPOLYHYDROXYSTEARATE; SORBITAN ISOSTEARATE; BHT; DISTEARDIMONIUM HECTORITE; SODIUM HYALURONATE; SODIUM ACETYLATED HYALURONATE; CITRIC ACID; PEG-9 DIGLYCIDYL ETHER/SODIUM HYALURONATE CROSSPOLYMER; ISODODECANE; MAGNESIUM STEARATE; ETHYLHEXYLGLYCERIN; MAGNESIUM POTASSIUM ALUMINOSILICATE FLUORIDE; PHENOXYETHANOL; ALLANTOIN; BIOSACCHARIDE GUM-1; ALOE BARBADENSIS LEAF; PENTYLENE GLYCOL; GLYCERIN; ETHYLHEXYL PALMITATE; POLYGLYCERYL-3 DIISOSTEARATE; 1,2-HEXANEDIOL; NIACINAMIDE; WATER; SPARASSIS CRISPA WHOLE

PURPOSE

Sunscreen

KEEP OUT OF REACH OF CHILDREN

lf prodluct is swallowed get medical help or contact a poison control center rigiht away.

QUESTIONS

1-212-244-5170 l info@amora.beauty

OTHER SAFETY INFORMATION

Protect the product in this container from excessive heat and direct sun.

DOSAGE AND ADMINISTRATION

Apply generously and evenly 15 minutes before sun exposure.

Reapply at least every 2 hours.

Use a water resistant sunscreen if swimming or sweating.

Children under 6 month: ask a doctor.

WARNINGS

For external use only.

Skin cancer/skin aging alert Spending time in the sun increases your risk of skin cancer and early skin aging.

This product has been shown only to help prevent sunburn, not skin cancer or early skin aging.

Do not use on damaged or broken skin.

When using this product keep out df eyes. rinse with water to remove.

Stop use and ask doctor if rash occurs.

Keep out of reach of children. m lf product is swallowed get medical help or contact a poison control center rigiht away.

INDICATIONS AND USAGE

Helps prevent sunburn.

ACTIVE INGREDIENT

Homosalate 10%, Octocrylene 8%, Octinoxate 6%, Octisalate 4% , Avobenzone 3%

INACTIVE INGREDIENT

WATER(AQUA)，GLYCERIN, ISODODECANE，ETHYLHEXYL PALMITATE，PEG-30 DIPOLYHYDROXYSTEARATE，SORBITAN ISOSTEARATE，POLYGLYCERYL-3 DIISOSTEARATE，ALUMINUM STARCH OCTENYLSUCCINATE，DISTEARDIMONIUM HECTORITE，MAGNESIUM STEARATE，PHENOXYETHANOL，GLYCERYL CAPRYLATE，SYNTHETIC FLUORPHLOGOPITE，ALLANTOIN，NIACINAMIDE，ETHYLHEXYLGLYCERIN，ALOE BARBADENSIS LEAF EXTRACT，BHT，TIN OXIDE，SPARASSIS CRISPA EXTRACT，SODIUM HYALURONATE，PENTYLENE GLYCOL，1,2-HEXANEDIOL，BIOSACCHARIDE GUM-1，SODIUM ACETYLATED HYALURONATE，SODIUM HYALURONATE CROSSPOLYMER，HYDROLYZED SODIUM HYALURONATE，CITRIC ACID，TITANIUM DIOXATE (CI 77891)